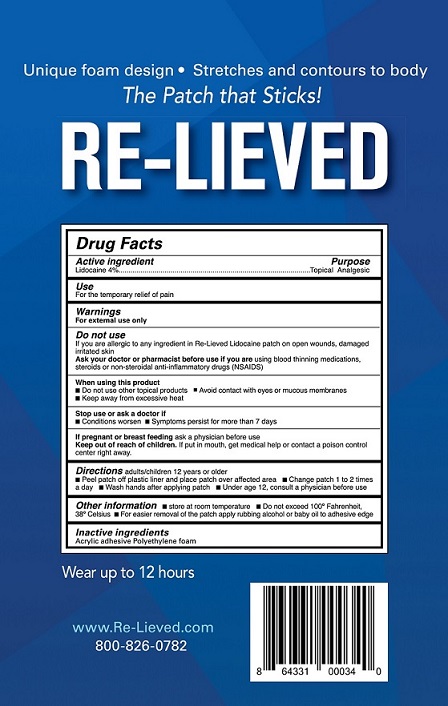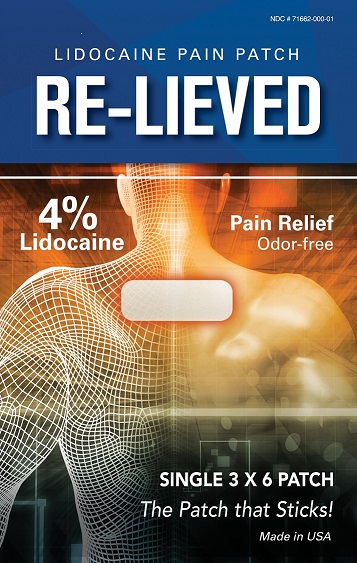 DRUG LABEL: Re-Lieved Lidocaine Patch
NDC: 71662-000 | Form: PATCH
Manufacturer: Transfer Technology
Category: otc | Type: HUMAN OTC DRUG LABEL
Date: 20250619

ACTIVE INGREDIENTS: LIDOCAINE 18 mg/116 cm2
INACTIVE INGREDIENTS: ACRYLIC ACID/ETHYLENE COPOLYMER (600 MPA.S); SILICON DIOXIDE

Re-Lieved Lidocaine 4% Patch: Five pouches in a plastic bag

Active Ingredient

Lidocaine 4%

Purpose

Topical Analgesic

Use

For the temporary relief of pain

Warnings

For external use only

Do not use

If you are allergic to any ingredient in Re-Lieved Lidocaine Patch, on open wounds or damaged irritated skin.

Ask your doctor or pharmacist before use if you are using blood thining medication, steroids, or non-steroidal anti-inflammatory drugs (NSAIDS)

When using this product

- do not use other topical products
- avoid contact with eyes or mucous membranes
- keep away from excessive heat

Stop use or ask a doctor if

- Condition worsens
- Symptons persist for more than seven days

PREGNANCY

If pregnant or breastfeeding ask a physican before use.

Keep out of reach of children. If put in mouth, get medical help or contact a poison control center right away.

DOSAGE AND ADMINISTRATION

Directions adults and children 12 years or older

- Peel patch off plastic liner and place patch over affected area.
- Change patch 1 to 2 times a day.
- Wash hands after applying patch
- Under age 12 consult a physician before use

Other information

- Store at room temperature
- Do not exceed 100o Fahrenheit 38o Celsius
- For easier removal of patch apply rubbing alcohol or baby oil to adhesive edge

Inactive ingredients: Acrylic adhesive, polyethylene foam